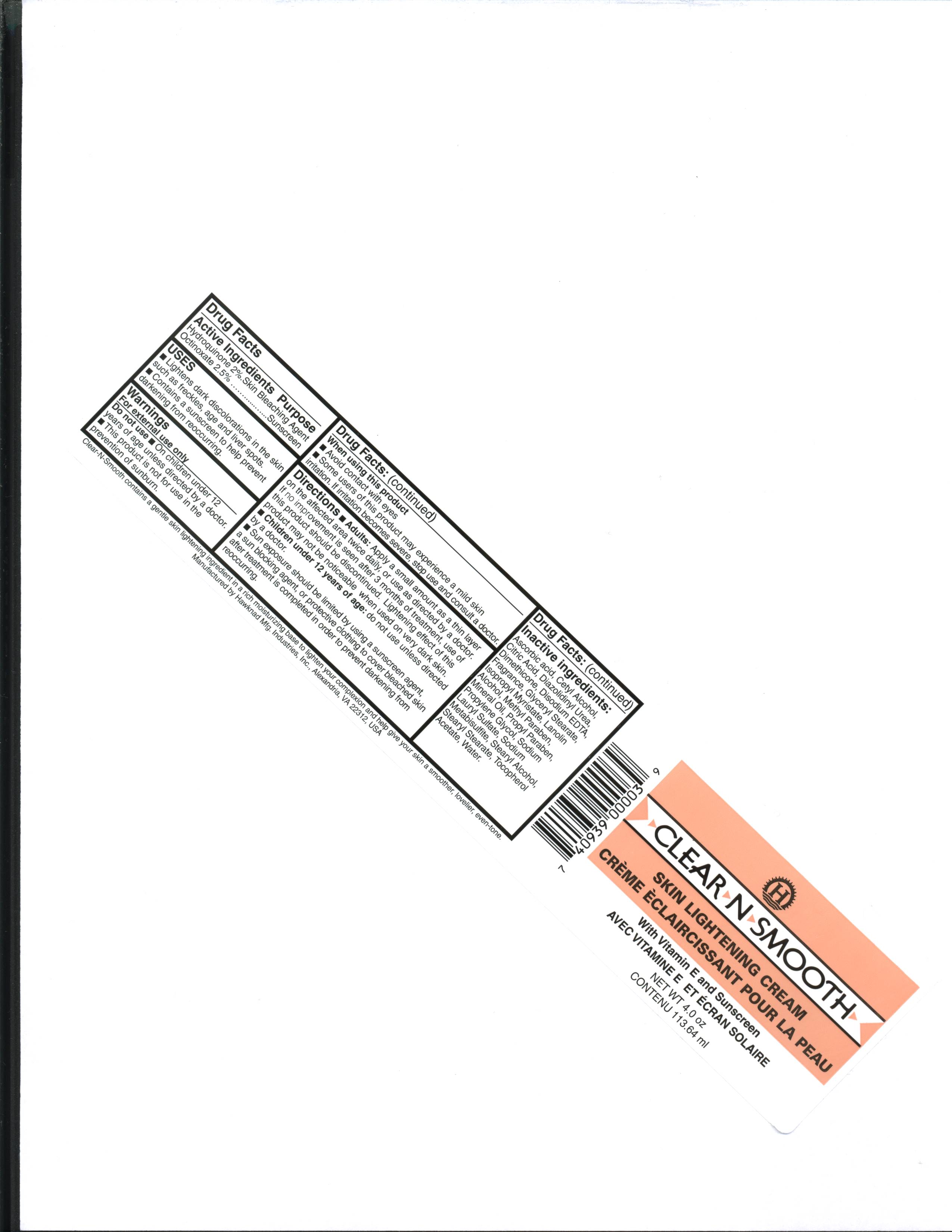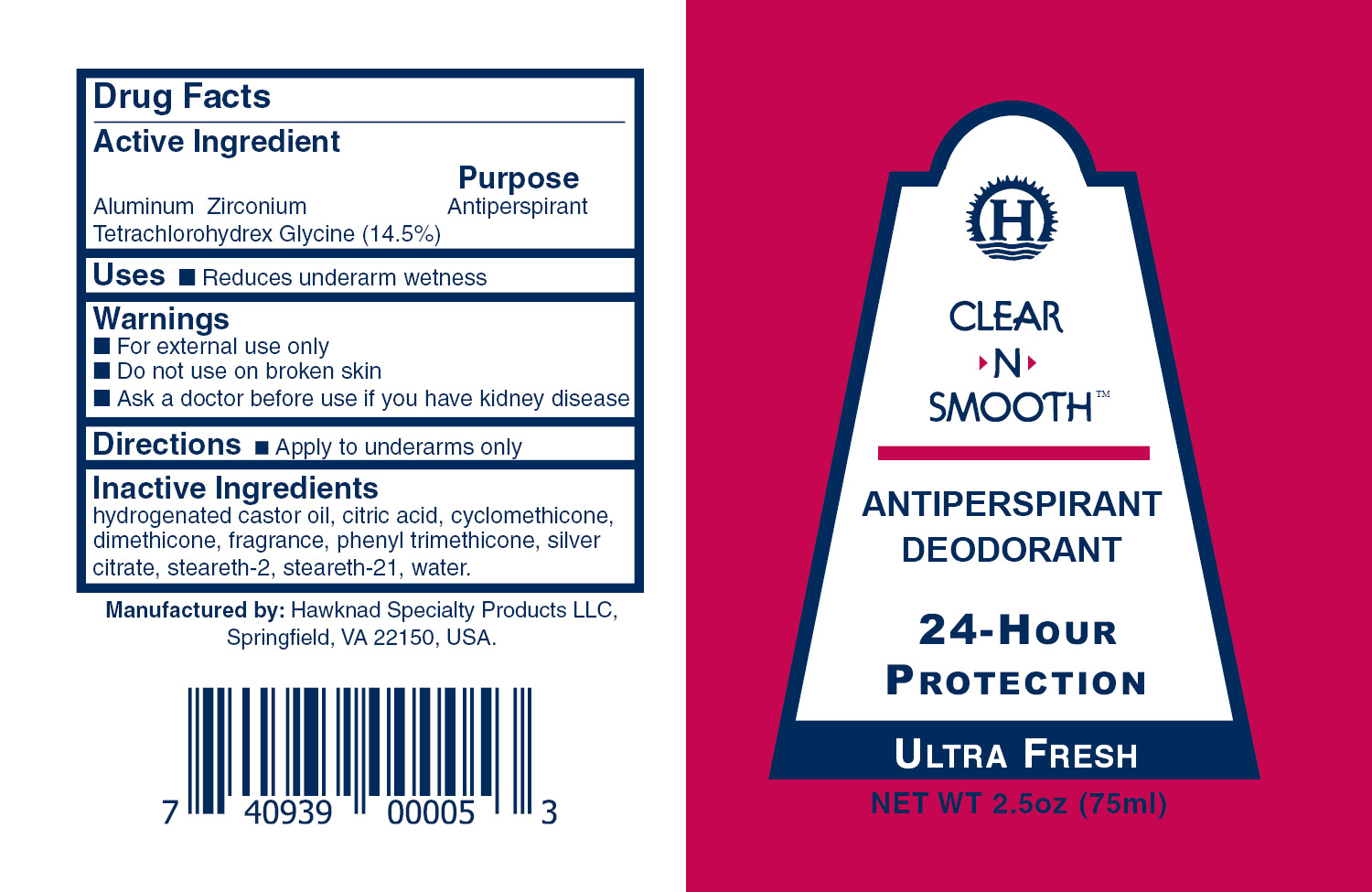 DRUG LABEL: Clear-N-Smooth
NDC: 76445-0055 | Form: LOTION
Manufacturer: Hawknad Manufacturing Industries
Category: otc | Type: HUMAN OTC DRUG LABEL
Date: 20211228

ACTIVE INGREDIENTS: ALUMINUM ZIRCONIUM TETRACHLOROHYDREX GLY 16 g/100 g
INACTIVE INGREDIENTS: DIMETHICONE 350 1 g/100 g; WATER 67.4 g/100 g; PHENOXYETHANOL 0.5 g/100 g; CAPRYLYL GLYCOL 0.25 g/100 g; HYDROGENATED CASTOR OIL 1 g/100 g; PHENYL TRIMETHICONE 1 g/100 g; STEARETH-2 3.75 g/100 g; STEARETH-21 1.85 g/100 g; CYCLOMETHICONE 5 g/100 g; PPG-15 STEARYL ETHER 1 g/100 g

Listing for Clear-N-Smooth Antiperspirant Lotion - Ultrafresh

Indications for Use

- Antiperspirant

Purpose

Reduce underarm wetness

Dosage

Apply to underarms only.

Keep Out of Reach of Children

Children under 12 years of age: do not use unless directed by a doctor.

Warnings

For external use only

Do not use on broken skin

Ask a doctor before use if you have kidney disease.

Instructions for Use

Tip ball and apply to underarm area only.

Inactive Ingredients

hydrogenated castor oil, cyclomethicone, dimethicone, ppg-15 stearyl ester, phenyl trimethicone, steareth-2, steareth-21, phenoxyethanol, capryly glycol, fragrance.

Active Ingredient

Aluminum Zirconium etrachlorohydrex Gly - 16%